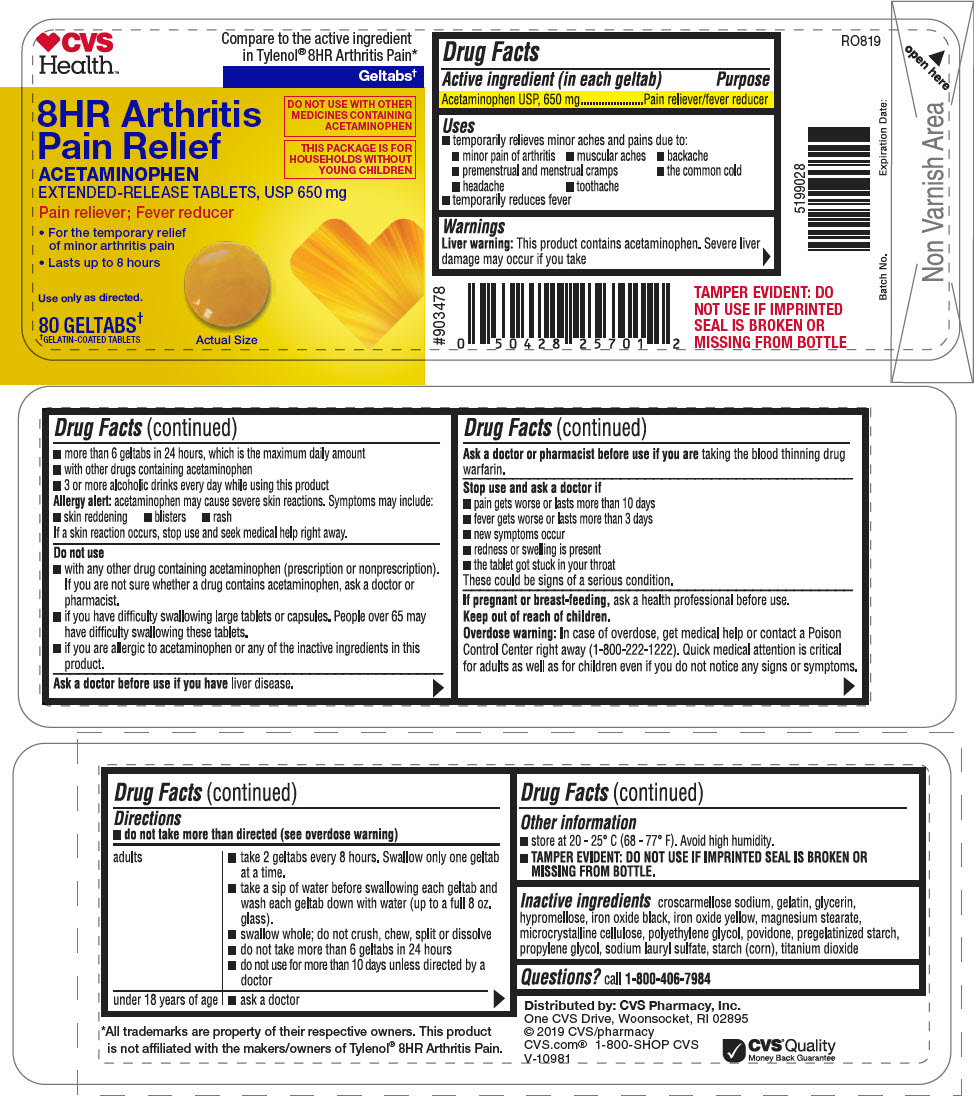 DRUG LABEL: Acetaminophen
NDC: 69842-930 | Form: TABLET, EXTENDED RELEASE
Manufacturer: CVS Pharmacy
Category: otc | Type: HUMAN OTC DRUG LABEL
Date: 20241227

ACTIVE INGREDIENTS: ACETAMINOPHEN 650 mg/1 1
INACTIVE INGREDIENTS: CROSCARMELLOSE SODIUM; GELATIN, UNSPECIFIED; GLYCERIN; HYPROMELLOSE, UNSPECIFIED; FERROSOFERRIC OXIDE; FERRIC OXIDE YELLOW; MAGNESIUM STEARATE; MICROCRYSTALLINE CELLULOSE; POLYETHYLENE GLYCOL, UNSPECIFIED; POVIDONE, UNSPECIFIED; STARCH, CORN; PROPYLENE GLYCOL; SODIUM LAURYL SULFATE; TITANIUM DIOXIDE

Acetaminophen

Drug Facts

Active ingredient (in each geltab)

Acetaminophen USP, 650 mg

Purpose

Pain reliever/fever reducer

Uses

- temporarily relieves minor aches and pains due to:
  - minor pain of arthritis
  - muscular aches
  - backache
  - premenstrual and menstrual cramps
  - the common cold
  - headache
  - toothache
- temporarily reduces fever

Warnings

Liver warning

This product contains acetaminophen. Severe liver damage may occur if you take

- more than 6 geltabs in 24 hours, which is the maximum daily amount
- with other drugs containing acetaminophen
- 3 or more alcoholic drinks every day while using this product

Allergy alert:acetaminophen may cause severe skin reactions. Symptoms may include:

- skin reddening
- blisters
- rash

If a skin reaction occurs, stop use and seek medical help right away.

Do not use

- with any other drug containing acetaminophen (prescription or nonprescription). If you are not sure whether a drug contains acetaminophen, ask a doctor or pharmacist.
- if you have difficulty swallowing large tablets or capsules. People over 65 may have difficulty swallowing these tablets.
- if you are allergic to acetaminophen or any of the inactive ingredients in this product.

Ask a doctor before use if you haveliver disease.

Ask a doctor or pharmacist before use if you aretaking the blood thinning drug warfarin.

Stop use and ask a doctor if

- pain gets worse or lasts more than 10 days
- fever gets worse or lasts more than 3 days
- new symptoms occur
- redness or swelling is present
- the tablet got stuck in your throat

These could be signs of a serious condition.

PREGNANCY OR BREAST FEEDING

If pregnant or breast-feeding,ask a health professional before use.

Keep out of reach of children.

Overdose warning

In case of overdose, get medical help or contact a Poison Control Center right away (1-800-222-1222). Quick medical attention is critical for adults as well as for children even if you do not notice any signs or symptoms.

Directions

- do not take more than directed (see overdose warning)

adults | - take 2 geltabs every 8 hours. Swallow only one geltab at a time. - take a sip of water before swallowing each geltab and wash each geltab down with water (up to a full 8 oz. glass). - swallow whole; do not crush, chew, split or dissolve - do not take more than 6 geltabs in 24 hours - do not use for more than 10 days unless directed by a doctor
under 18 years of age | - ask a doctor

Other information

- store at 20 - 25° C (68 - 77° F). Avoid high humidity.
- TAMPER EVIDENT: DO NOT USE IF IMPRINTED SEAL IS BROKEN OR MISSING FROM BOTTLE.

Inactive ingredients

croscarmellose sodium, gelatin, glycerin, hypromellose, iron oxide black, iron oxide yellow, magnesium stearate, microcrystalline cellulose, polyethylene glycol, povidone, pregelatinized starch, propylene glycol, sodium lauryl sulfate, starch (corn), titanium dioxide

Questions?

call 1-800-406-7984

Distributed by: CVS Pharmacy, Inc.
One CVS Drive, Woonsocket, RI 02895

PRINCIPAL DISPLAY PANEL - 650 mg Tablet Bottle Label

CVS
HEALTH™

Compare to the active ingredient
in Tylenol®8HR Arthritis Pain*

Geltabs†

8HR Arthritis
Pain Relief
ACETAMINOPHEN
EXTENDED-RELEASE TABLETS, USP 650 mg

DO NOT USE WITH OTHER
MEDICINES CONTAINING
ACETAMINOPHEN

THIS PACKAGE IS FOR
HOUSEHOLDS WITHOUT
YOUNG CHILDREN

Pain reliever; Fever reducer

- For the temporary relief
  of minor arthritis pain
- Lasts up to 8 hours

Use only as directed.

80 GELTABS†
†GELATIN-COATED TABLETS

Actual Size